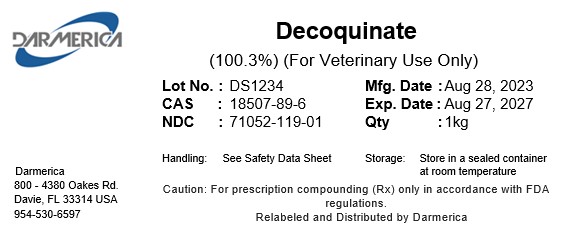 DRUG LABEL: Decoquinate
NDC: 71052-119 | Form: POWDER
Manufacturer: DARMERICA, LLC
Category: other | Type: BULK INGREDIENT - ANIMAL DRUG
Date: 20250411

ACTIVE INGREDIENTS: DECOQUINATE 1 kg/1 kg

Decoquinate